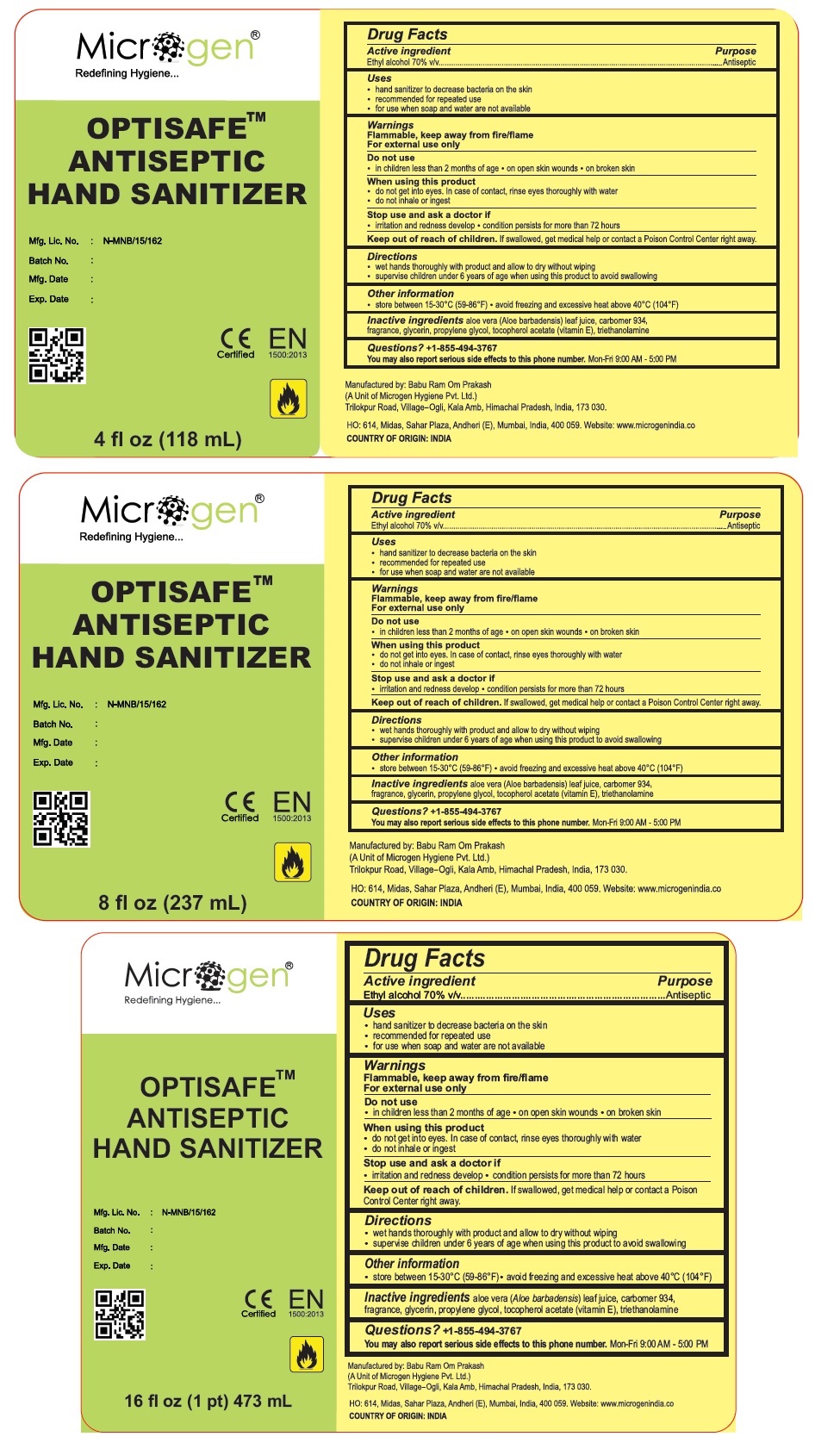 DRUG LABEL: OPTISAFE ANTISEPTIC HAND SANITIZER
NDC: 75043-060 | Form: GEL
Manufacturer: BABU RAM OM PRAKASH
Category: otc | Type: HUMAN OTC DRUG LABEL
Date: 20200505

ACTIVE INGREDIENTS: ALCOHOL 70 mL/100 mL
INACTIVE INGREDIENTS: ALOE VERA LEAF; CARBOMER HOMOPOLYMER TYPE B (ALLYL SUCROSE CROSSLINKED); GLYCERIN; PROPYLENE GLYCOL; .ALPHA.-TOCOPHEROL ACETATE; TROLAMINE

OPTISAFE ANTISEPTIC HAND SANITIZER

Active ingredient

Ethyl alcohol 70% v/v

Purpose

Antiseptic

Uses

- hand sanitizer to decrease bacteria on the skin
- recommended for repeated use
- for use when soap and water are not available

Warnings

Flammable, keep away from fire/flame.

For external use only

Do not use

• in children less than 2 months of age • on open skin wounds • on broken skin

When using this product

• do not get into eyes. In case of contact, rinse eyes thoroughly with water.

• do not inhale or ingest.

Stop use and ask a doctor if

• irritation and redness develop • condition persists for more than 72 hours

Keep out of reach of children. If swallowed, get medical help or contact a Poison Control Center right away.

Directions

• wet hands thoroughly with product and allow to dry without wiping
• supervise children under 6 years of age when using this product to avoid swallowing

Other information

• store between 15-30°C (59-86°F)

• avoid freezing and excessive heat above 40°C (104°F)

Inactive ingredients

aloe vera (Aloe barbadensis) leaf juice, carbomer 934, fragrance, glycerin, propylene glycol, tocopherol acetate (vitamin E), triethanolamine

Questions? +1-855-494-3767

You may also report serious side effects to this phone number. Mon-Fri 9.00 AM - 5.00 PM

Microgen®

Redefining Hygiene...

Manufactured by: Babu Ram Om Prakash
(A Unit of Microgen Hygiene Pvt. Ltd.)
Trilokpur Road, Village-Ogli, Kala Amb, Himachal Pradesh, India, 173 030

HO: 614, Midas, Sahar Plaza, Andheri(E), Mumbai, India, 400 059. Website: www.microgenindia.co

COUNTRY OF ORIGIN: INDIA